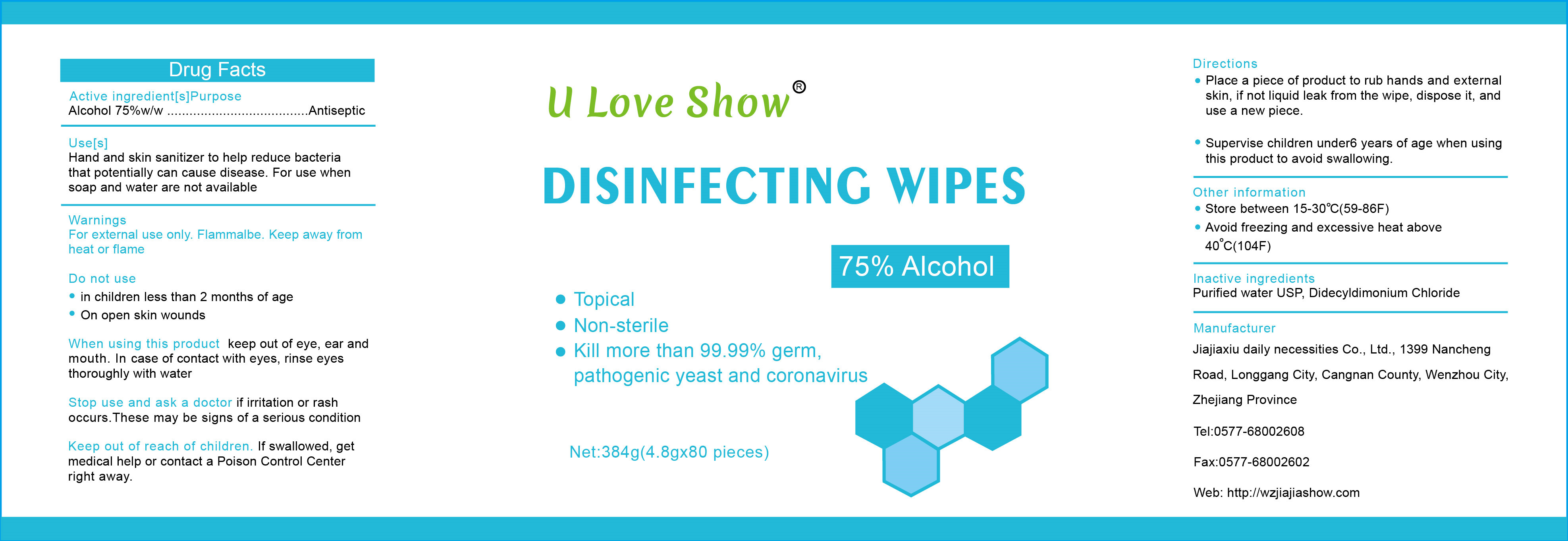 DRUG LABEL: DISINFECTING WIPES
NDC: 84287-001 | Form: CLOTH
Manufacturer: Wenzhou Jiajia show Daily Necessities Co., Ltd
Category: otc | Type: HUMAN OTC DRUG LABEL
Date: 20210111

ACTIVE INGREDIENTS: ALCOHOL 75 mL/100 mL
INACTIVE INGREDIENTS: DIDECYLDIMONIUM CHLORIDE; WATER

ACTIVE INGREDIENT

Alcohol 75%

PURPOSE

Antiseptic

Use[s]

Hand and skin sanitizer to help reduce bacteriathat potentially can cause disease.For use when soap and water are not available

WARNINGS

For external use only. Flammalbe. Keep away from heat or flame

DO NOT USE

in children less than 2 months of age
on open skin wounds

When using this product keep out of eye, ear and mouth. In case of contact with eyes, rinse eyesthoroughly with water

Stop use and ask a doctor if irritation or rash occurs.These may be signs of a serious condition

Keep out of reach of children. lf swallowed, get medical help or contact a Poison Control Center right away.

Directions

Place a piece of product to rub hands and external skin, if not liquid leak from the wipe, dispose it, and use a new piece.
Supervise children under 6 years of age when usingthis product to avoid swallowing.

HOW SUPPLIED

Store between 15-30°C(59-86°F)
Avoid freezing and excessive heat above40°C(104°F)

INACTIVE INGREDIENT

Purified water USP, Didecyldimonium Chloride